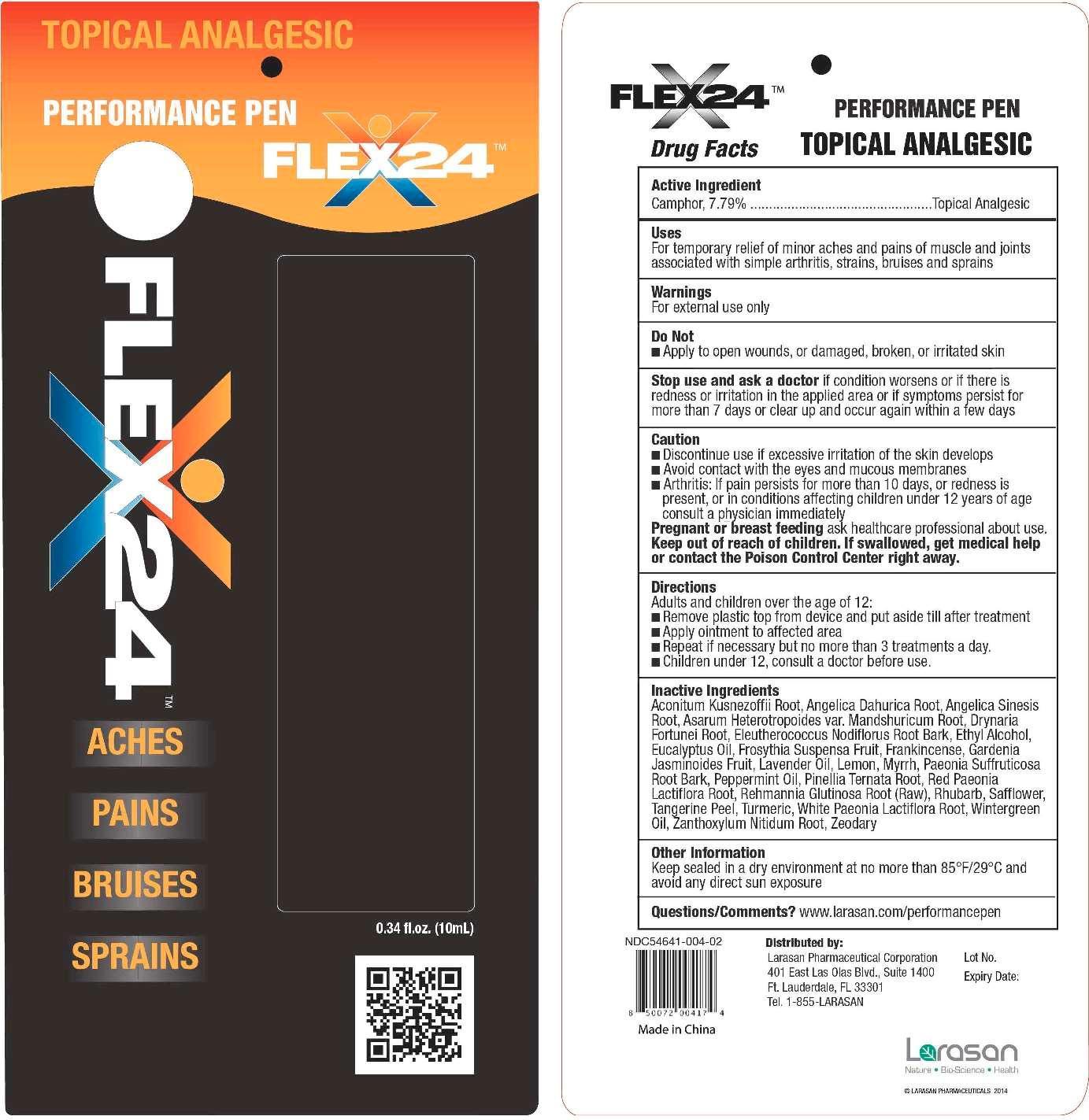 DRUG LABEL: Flex24 Performance Pen
NDC: 54641-004 | Form: LIQUID
Manufacturer: Larasan Pharmaceutical Corporation
Category: otc | Type: HUMAN OTC DRUG LABEL
Date: 20191208

ACTIVE INGREDIENTS: CAMPHOR (NATURAL) 7.79 g/100 mL
INACTIVE INGREDIENTS: ANGELICA DAHURICA ROOT; ACONITUM KUSNEZOFFII ROOT; ANGELICA SINENSIS ROOT; ASARUM HETEROTROPOIDES VAR. MANDSHURICUM ROOT; DRYNARIA FORTUNEI ROOT; ELEUTHEROCOCCUS NODIFLORUS ROOT BARK; ALCOHOL; EUCALYPTUS OIL; FORSYTHIA SUSPENSA FRUIT; FRANKINCENSE; GARDENIA JASMINOIDES FRUIT; LAVENDER OIL; LEMON; MYRRH; PAEONIA SUFFRUTICOSA ROOT BARK; PEPPERMINT OIL; PINELLIA TERNATA ROOT; PAEONIA LACTIFLORA ROOT; REHMANNIA GLUTINOSA ROOT; RHUBARB; SAFFLOWER; TANGERINE PEEL; TURMERIC; METHYL SALICYLATE; ZANTHOXYLUM NITIDUM ROOT; ZEDOARY

Active Ingredient

Camphor, 7.79%

Purpose

Topical analgesic

Uses

For temporary relief of minor aches and pains of muscle and joints associated with simple arthritis, strains, bruises and sprains

Warnings

For external use only

Do not

apply to open wounds, or damaged, broken, or irritated skin

Stop use and ask a doctor

if condition worsens or if there is redness or irritation in the applied area or if symptoms persist for more than 7 days or clear up and occur again within a few days

Caution

- Discontinue use if excessive irritation of the skin develops
- Avoid contact with the eyes and mucous membranes
- Arthritis: If pain persists for more than 10 days, or redness is present, or in conditions affecting children under 12 years of age consult a physician immediately

Pregnant or breast feeding

ask healthcare professional about use

Keep out of reach of children

If swallowed, get medical help or contact a Poison Control Center right away

Directions

Adults and children over the age of 12:

- Remove plastic top from device and put aside till after treatment
- Apply ointment to affected area
- Repeat if necessary but no more than 3 treatments a day.

Children under 12, consult a doctor before use.

Inactive Ingredients

Aconitum kusnezoffii root, Angelica dahurica root, Angelica sinesis root, Asarum heterotropoides var. mandshuricum root, Drynaria fortunei root, Eleutherococcus nodiflorus root bark, Ethyl alcohol, Eucalyptus oil, Frosythia suspensa fruit, Frankincense, Gardenia jasminoides fruit, Lavender oil, Lemon, Myrrh, Paeonia suffruticosa root bark, Peppermint oil, Pinellia ternata root, Red paeonia lactiflora root, Rhemannia glutinosa root (raw), Rhubarb, Safflower, Tangerine peel, Turmeric, White paeonia lactiflora root, Wintergreen oil, Zanthoxylum nitidum root, Zeodary

Other Information

Keep sealed in a dry environment at no more than 85°F/29°C and avoid any direct sun exposure

Questions/Comments?

www.larasan.com/performancepen

Distributed By:

Larasan Pharmaceutical Corporation

401 East Las Olas Blvd., Suite 1400

Ft. Lauderdale, FL 33301

Tel. 1-855-LARASAN

NDC 54641-004-02

Made in China

Flex24™ Performance Pen

Topical Analgesic

Aches Pains Bruises Sprains

0.34 fl. oz. (10 mL)